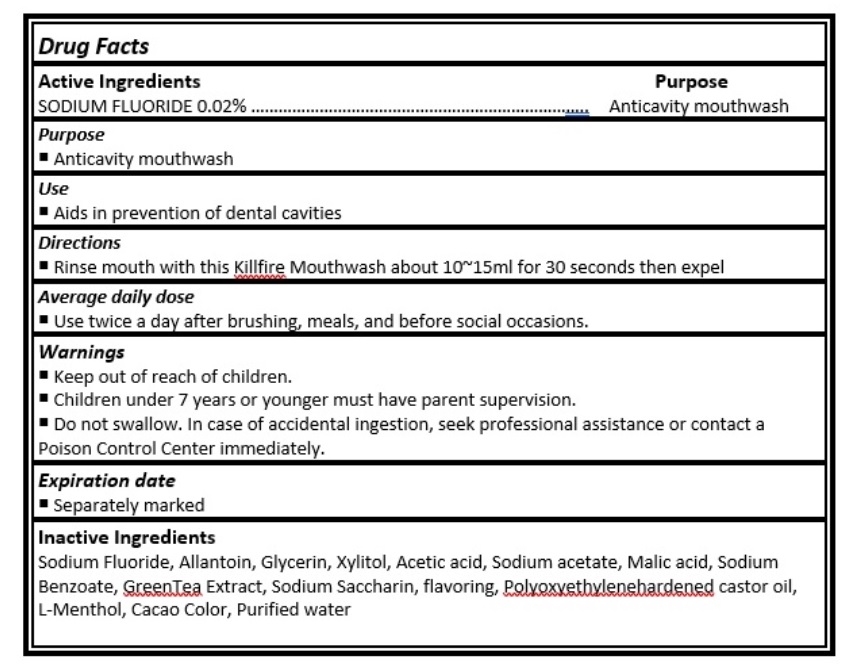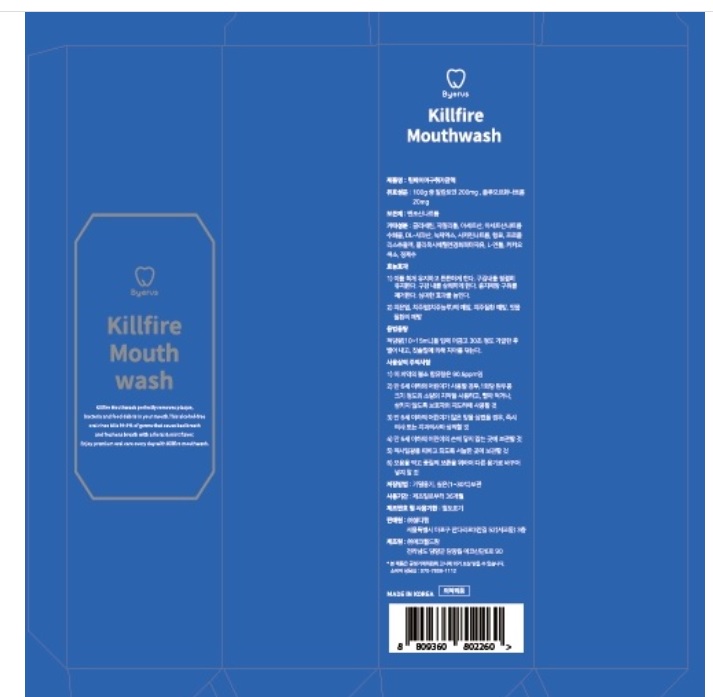 DRUG LABEL: Killfire Mouthwash
NDC: 24765-132 | Form: RINSE
Manufacturer: Pharmacal-International. Co., Ltd.
Category: otc | Type: HUMAN OTC DRUG LABEL
Date: 20241025

ACTIVE INGREDIENTS: SODIUM FLUORIDE 0.02 g/100 mL
INACTIVE INGREDIENTS: ALLANTOIN; GLYCERIN; XYLITOL; ACETIC ACID; SODIUM ACETATE; MALIC ACID; SODIUM BENZOATE; GREEN TEA LEAF; SACCHARIN SODIUM ANHYDROUS; POLYOXYL 35 CASTOR OIL; RACEMENTHOL; PROPOLIS WAX; WATER

Active ingredient

Sodium Fluoride (0.02%)

Purpose

- Anticavity mouthwash

Use

- Aids in prevention of dental cavities

Directions

- Rinse mouth with this Killfire Mouthwash about 10~15ml for 30 seconds then expel

Average daily dose

- Use twice a day after brushing, meals, and before social occasions.

Warnings

- Keep out of reach of children.
- Children under 7 years or younger must have parent supervision.
- Do not swallow. In case of accidental ingestion, seek professional assistance or contact a Poison Control Center immediately.

Inactive Ingredients

Sodium Fluoride, Allantoin, Glycerin, Xylitol, Acetic acid, Sodium acetate, Malic acid, Sodium Benzoate, GreenTea Extract, Sodium Saccharin, flavoring, Polyoxyethylenehardened castor oil, L-Menthol, Cacao Color, Purified water